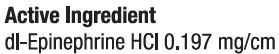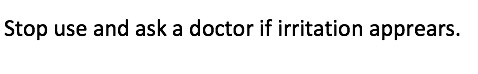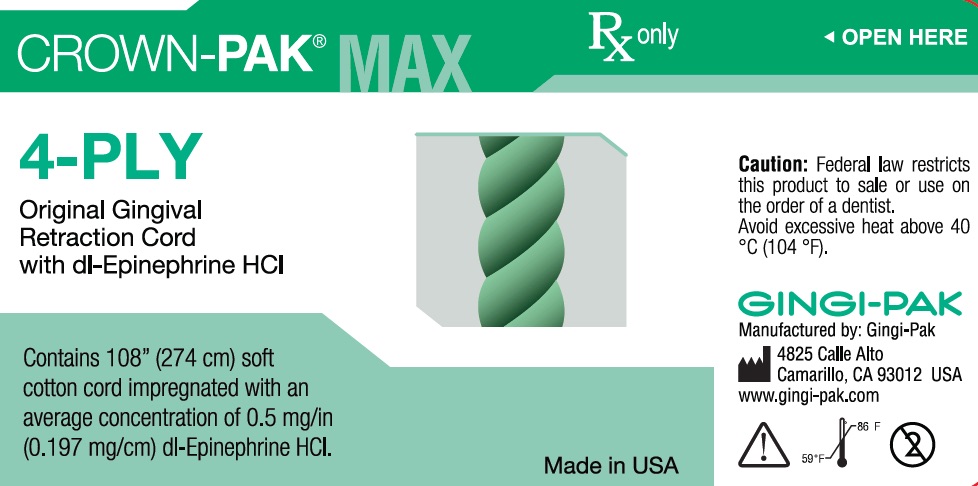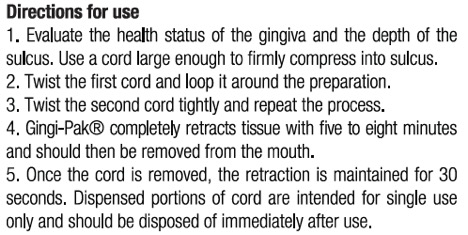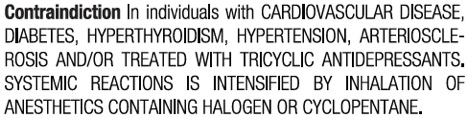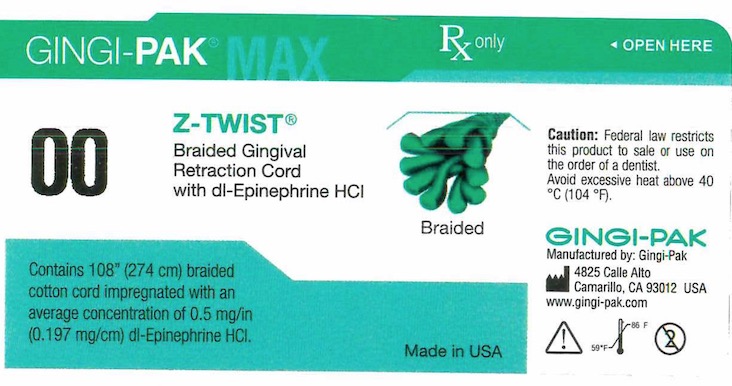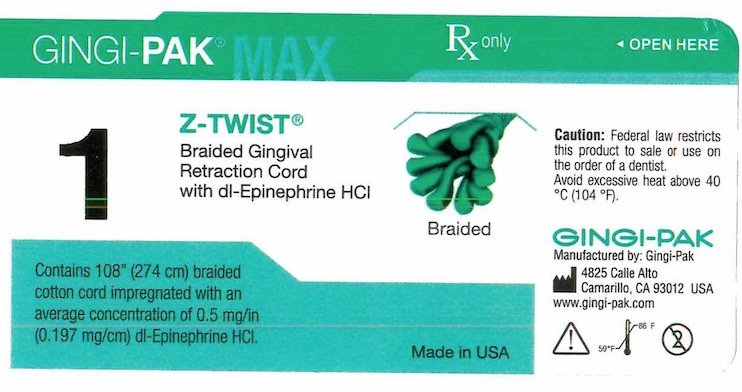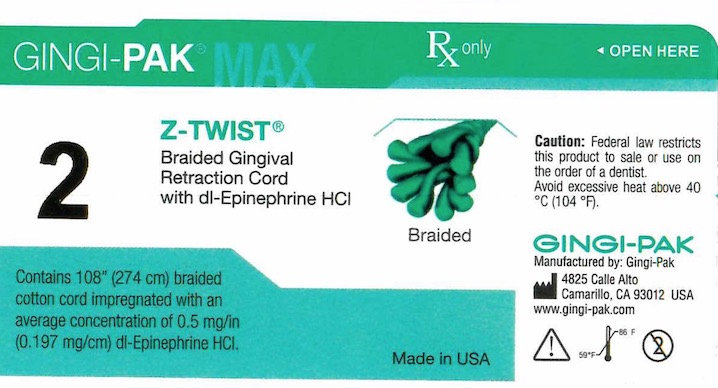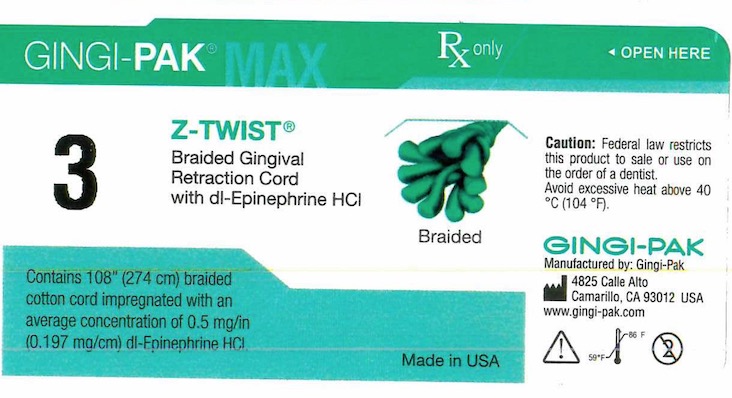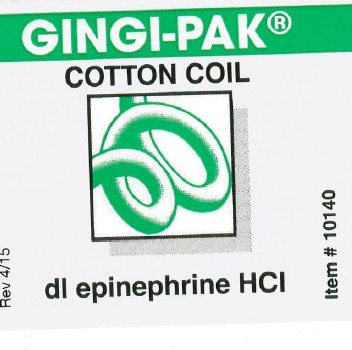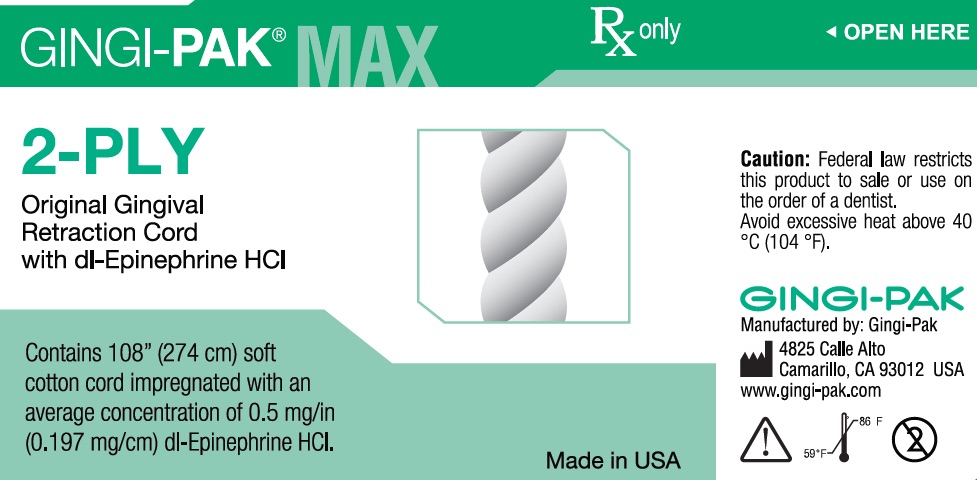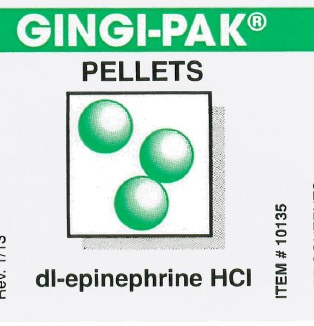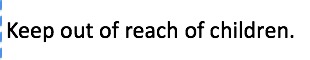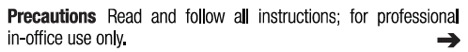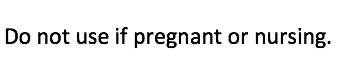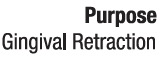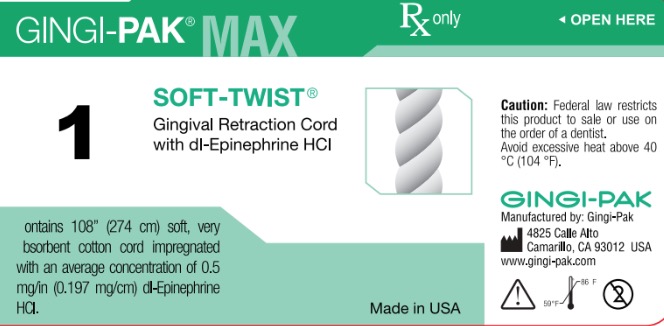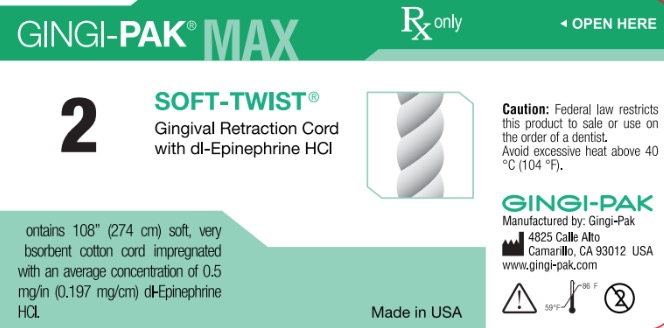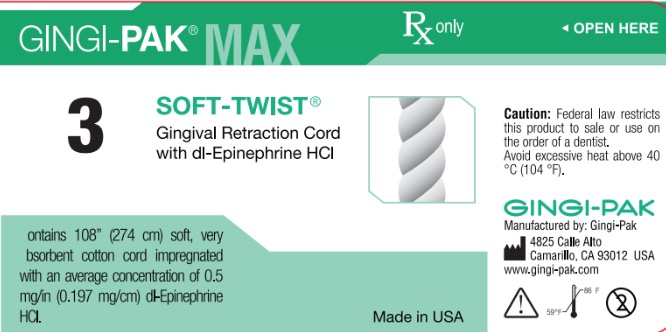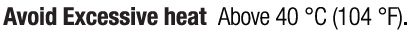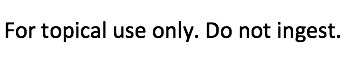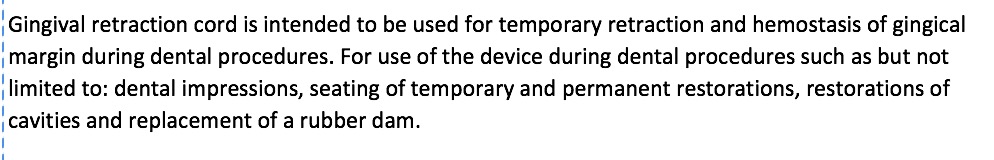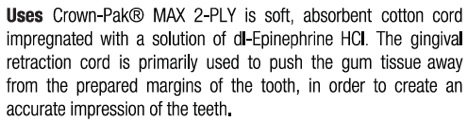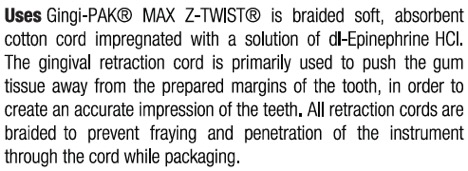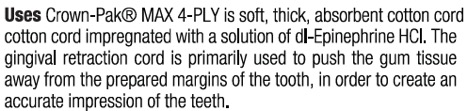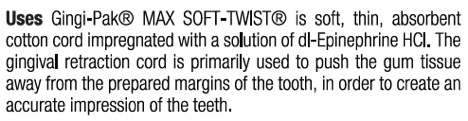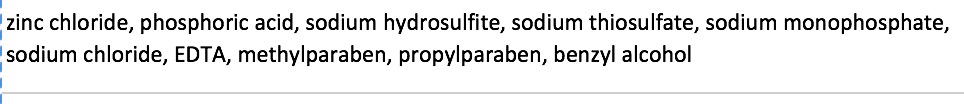 DRUG LABEL: GINGI-PAK MAX SOFT-TWIST NO 1
NDC: 10129-001 | Form: SOLUTION
Manufacturer: Gingi-Pak a Division of the Belport
Category: otc | Type: HUMAN OTC DRUG LABEL
Date: 20181221

ACTIVE INGREDIENTS: EPINEPHRINE HYDROCHLORIDE 0.197 mg/10 mm
INACTIVE INGREDIENTS: COTTON FIBER 10 mm/10 mm; SODIUM DITHIONITE 6.15 ug/10 mm; EDETIC ACID 0.033 ug/10 mm; METHYLPARABEN 1.65 ug/10 mm; PROPYLPARABEN 0.813 ug/10 mm; SODIUM CHLORIDE 8.13 ug/10 mm; SODIUM THIOSULFATE 2.46 ug/10 mm; SODIUM PHOSPHATE, MONOBASIC 6.15 ug/10 mm

Gingi-Pak Retraction Cord